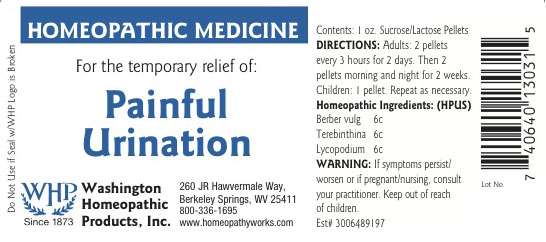 DRUG LABEL: Painful Urination
NDC: 68428-014 | Form: PELLET
Manufacturer: Washington Homeopathic Products
Category: homeopathic | Type: HUMAN OTC DRUG LABEL
Date: 20151230

ACTIVE INGREDIENTS: BERBERIS VULGARIS ROOT BARK 6 [hp_C]/1 1; TURPENTINE OIL 6 [hp_C]/1 1; LYCOPODIUM CLAVATUM SPORE 6 [hp_C]/1 1
INACTIVE INGREDIENTS: SUCROSE; LACTOSE

DRUG FACTS

ACTIVE INGREDIENTS

BERBER VULG 6C

TEREBINTHINA 6C

LYCOPODIUM 6C

USES

To relieve the symptoms of ache in the small of the back, frequent urge to urinate but passing only a small amount of urine.

KEEP OUT OF REACH OF CHILDREN

Keep this and all medicines out of reach of children.

INDICATIONS

BERBER VULG Skin inflammation

TEREBINTHINA Urinary symptoms

LYCOPODIUM Digestion

STOP USE AND ASK DOCTOR

If symptoms persist/worsen or if pregnant/nursing, stop use and consult your practitioner.

DIRECTIONS

Adults 2 pellets every 3 hours for 2 days. Then 2 pellets morning and night for 2 weeks.

Children: 1 pellet. Repeat as necessary.

INACTIVE INGREDIENTS

Sucrose/Lactose

PRINCIPAL DISPLAY PANEL

Enter section text here